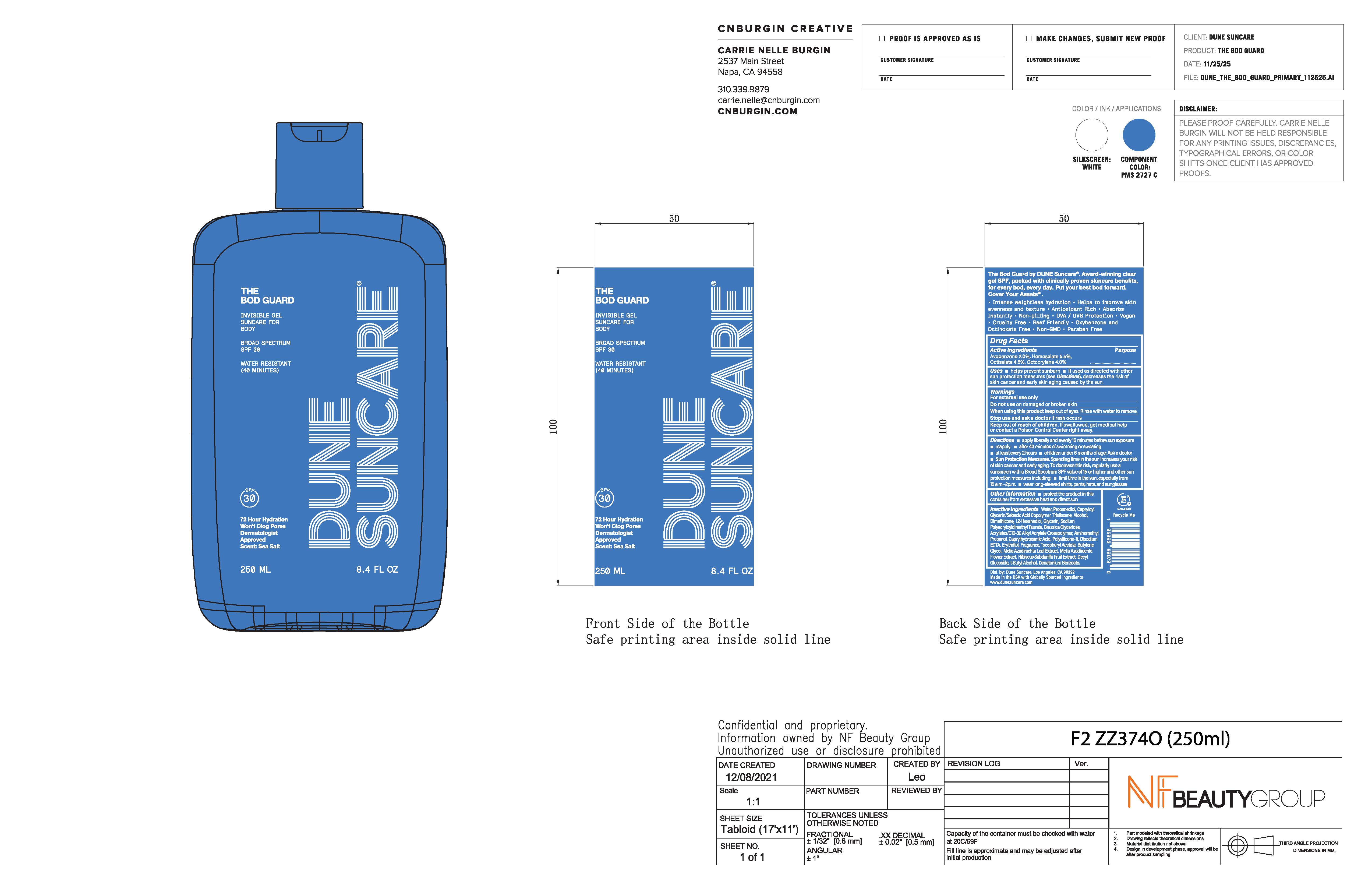 DRUG LABEL: THE BOD GUARD
NDC: 82757-200 | Form: GEL
Manufacturer: Dune Suncare, Inc.
Category: otc | Type: HUMAN OTC DRUG LABEL
Date: 20251218

ACTIVE INGREDIENTS: AVOBENZONE 20 mg/1 mL; HOMOSALATE 55 mg/1 mL; OCTISALATE 45 mg/1 mL; OCTOCRYLENE 40 mg/1 mL
INACTIVE INGREDIENTS: POLYSILICONE-15; TERT-BUTYL ALCOHOL; BRASSICA NAPUS OIL; BUTYLENE GLYCOL; DENATONIUM BENZOATE; GLYCERIN; ACRYLATES/C10-30 ALKYL ACRYLATE CROSSPOLYMER (60000 MPA.S); MAGNESIUM DISODIUM EDTA; CAPRYLHYDROXAMIC ACID; ERYTHRITOL; FRAGRANCE 13576; AMINOMETHYL PROPANOL; DIMETHICONE; ALPHA-TOCOPHEROL ACETATE; WATER; PROPANEDIOL; CAPRYLOYL GLYCERIN/SEBACIC ACID COPOLYMER (2000 MPA.S); TRISILOXANE; ALCOHOL; SODIUM POLYACRYLOYLDIMETHYL TAURATE; 1,2-HEXANEDIOL; MELIA AZADIRACHTA LEAF; AZADIRACHTA INDICA FLOWER; HIBISCUS SABDARIFFA WHOLE; DECYL GLUCOSIDE

THE BOD GUARD

Active Ingredients

Avobenzone 2.0%

Homosalate 5.5%

Octisalate 4.5%

Octocrylene 4.0%

Purpose

Sunscreen

Uses

- helps prevent sunburn
- If used as directed with other sun protection measures (see Directions), decreases the risk of skin cancer and early skin aging caused by the sun

Warnings

For external use only

Do not use on damaged or broken skin

When using this product keep out of eyes. Rinse with water to remove.

Stop use and ask a doctor if rash occurs

Keep out of reach of children. If swallowed, get medical help or contact a Poison Control Center right away.

Do not use

on damaged or broken skin

When using this product

keep out of eyes. Rinse with water to remove.

Stop use and ask a doctor

if rash occurs

Keep out of reach of children.

If swallowed, get medical help or contact a Poison Control Center right away.

Directions

- apply liberally and evenly 15 minutes before sun exposure
- reapply:
  - after 40 minutes of swimming or sweating
  - at least every 2 hours
  - children under 6 months: Ask a doctor
- Sun Protection Measures. Spending time in the sun increases your risk of skin cancer and early aging. To decrease this risk, regularly use a sunscreen with Broad Spectrum SPF value of 15 or higher and other sun protection measures including:
- limit time in the sun, especially from 10 a.m.–2 p.m.
- wear long-sleeve shirts, pants, hats, and sunglasses

Other information

- protect the product in this container from excessive heat and direct sun

Inactive ingredients

Water, Propanediol, Capryloyl Glycerin/Sebacic Acid Copolymer, Trisiloxane, Alcohol, Dimethicone, 1,2-Hexanediol, Glycerin, Sodium Polyacryloyldimethyl Taurate, Brassica Glycerides, Acrylates C10-30 Alkyl Acrylate Crosspolymer, Aminomethyl Propanol, Caprylhydroxamic Acid, Polysilicone-11, Disodium EDTA, Erythritol, Fragrance, Tocopheryl Acetate, Butylene Glycol, Melia Azadirachta Leaf Extract, Melia Azadirachta Flower Extract, Hibiscus Sabdariffa Fruit Extract, Decyl Glucoside, t-Butyl Alcohol, Denatonium Benzoate.

Principal Display Panel

DUNE SUNCARE

THE BOD GUARD

INVISIBLE GEL

SUNCARE FOR

BODY

BROAD SPECTRUM

SPF 30

WATER RESISTANT

(40 MINUTES)

72 Hour Hydration
Won't Clog Pores

Dermatologist

Approved

Scent: Sea Salt

250 mL

8.4 FL OZ